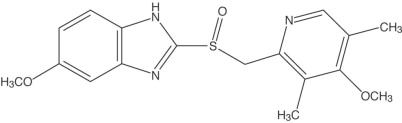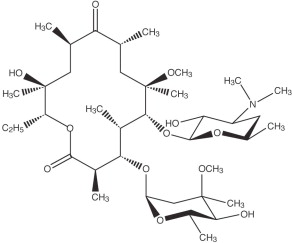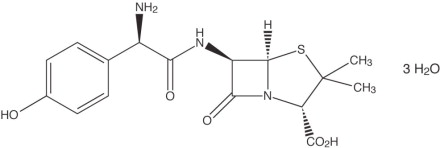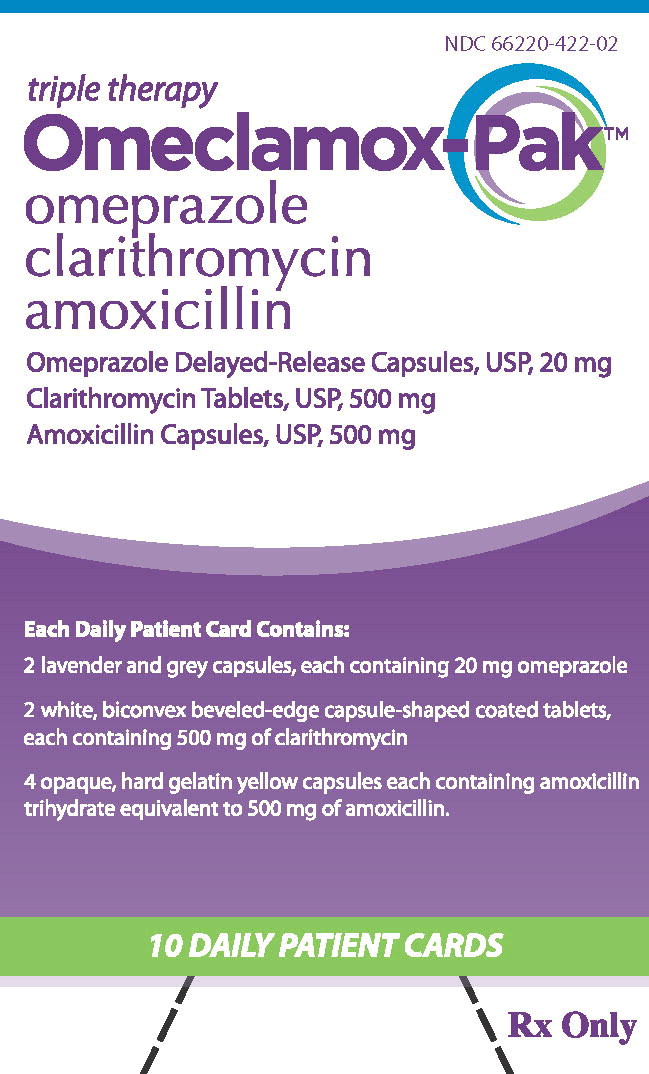 DRUG LABEL: Omeclamox-Pak

NDC: 66220-422 | Form: KIT | Route: ORAL
Manufacturer: Cumberland Pharmaceuticals Inc.
Category: prescription | Type: HUMAN PRESCRIPTION DRUG LABEL
Date: 20230817

ACTIVE INGREDIENTS: OMEPRAZOLE
 20 mg/1 1; CLARITHROMYCIN
 500 mg/1 1; AMOXICILLIN
 500 mg/1 1
INACTIVE INGREDIENTS: CROSPOVIDONE; HYPROMELLOSES; LACTOSE, UNSPECIFIED FORM; MAGNESIUM STEARATE; MANNITOL; MEGLUMINE; METHACRYLIC ACID - METHYL METHACRYLATE COPOLYMER (1:1); PEG/PPG-30/160 COPOLYMER; POVIDONE; ETHYL ACETATE; D&C RED NO. 28; FD&C BLUE NO. 1; FD&C RED NO. 40; FD&C YELLOW NO. 6; FERRIC OXIDE YELLOW; GELATIN; SILICON DIOXIDE; SODIUM LAURYL SULFATE; TITANIUM DIOXIDE; CROSCARMELLOSE SODIUM; HYPROMELLOSE 2208 (100 MPA.S); LACTOSE MONOHYDRATE; MAGNESIUM STEARATE; CELLULOSE, MICROCRYSTALLINE; POLYDEXTROSE; POLYETHYLENE GLYCOL, UNSPECIFIED; POVIDONE; STEARIC ACID; TALC; TITANIUM DIOXIDE; TRIACETIN; MAGNESIUM STEARATE; SODIUM LAURYL SULFATE; D&C RED NO. 33; FD&C BLUE NO. 1; FD&C RED NO. 40; FD&C YELLOW NO. 6; GELATIN; TITANIUM DIOXIDE

HIGHLIGHTS OF PRESCRIBING INFORMATION

These highlights do not include all the information needed to use OMECLAMOX®-PAK safely and effectively. See full prescribing information for OMECLAMOX-PAK.
OMECLAMOX-PAK (omeprazole delayed-release capsules; clarithromycin tablets, amoxicillin capsules) co-packaged for oral use
Initial U.S. Approval: 2011

RECENT MAJOR CHANGES

Contraindications (4.2) | 08/2023

1 INDICATIONS AND USAGE

OMECLAMOX-PAK, a co-packaged product containing omeprazole, a proton pump inhibitor, clarithromycin, a macrolide antimicrobial, and amoxicillin, a penicillin class antibacterial, is indicated for the treatment of patients with Helicobacter pylori infection and duodenal ulcer disease (active or up to one-year history) to eradicate H. pylori. (1)

To reduce the development of drug-resistant bacteria and maintain the effectiveness of OMECLAMOX-PAK and other antibacterial drugs, OMECLAMOX-PAK should be used only to treat or prevent infections that are proven or strongly suspected to be caused by bacteria. (1.2)

2 DOSAGE AND ADMINISTRATION

- Adult regimen: omeprazole 20 mg plus clarithromycin 500 mg plus amoxicillin 1000 mg, each given twice daily for 10 days in the morning and evening before eating a meal. (2)
- Advise patients to swallow all tablets and capsules whole. (2)
- In patients with an ulcer present at initiation of therapy, an additional 18 days of omeprazole 20 mg once daily is recommended. (2)

3 DOSAGE FORMS AND STRENGTHS

Pack of 10 daily administration cards for morning and evening dosing, each containing (3):

- Two omeprazole delayed-release capsules, USP, 20 mg.
- Two clarithromycin tablets, USP, 500 mg.
- Four amoxicillin capsules, USP, 500 mg.

4 CONTRAINDICATIONS

- Known hypersensitivity to omeprazole, any macrolide antibiotic, any penicillin, or any component of the formulations. (4.1)
- Coadministration with pimozide, lurasidone, ergotamine or dihydroergotamine. (4.2, 7.2, 7.3)

5 WARNINGS AND PRECAUTIONS

- Embryo-Fetal Toxicity: Based on animal findings for omeprazole and clarithromycin, OMECLAMOX-PAK may cause fetal harm. OMECLAMOX-PAK is not recommended for use in pregnant women except in clinical circumstances when there is no appropriate alternative therapy. (5.1)
- Severe Cutaneous Adverse Reactions: Discontinue at the first signs or symptoms of severe cutaneous adverse reactions or other signs of hypersensitivity and consider further evaluation. (5.2)
- Colchicine interaction: Concomitant use of clarithromycin and colchicine has resulted in deaths, especially in the elderly with renal insufficiency. Monitor patients for clinical symptoms of colchicine toxicity. (5.3, 7.1)
- Myasthenia gravis: Exacerbation of symptoms and new onset of symptoms reported with clarithromycin. Monitor patients for symptoms. (5.4)
- Clostridioides difficile-associated diarrhea: Reported with use of clarithromycin and amoxicillin; evaluate if diarrhea occurs. (5.5)
- Risk of gastric malignancy: Symptomatic response does not preclude concomitant underlying malignancy. (5.6)
- Acute Tubulointerstitial Nephritis: has been observed in patients taking proton pump inhibitors (PPIs), including omeprazole. Discontinue OMECLAMOX-PAK and evaluate patients (5.7)
- Cutaneous and Systemic Lupus Erythematosus: Mostly cutaneous; new onset or exacerbation of existing disease; discontinue OMECLAMOX- PAK and evaluate (5.8)

6 ADVERSE REACTIONS

Most frequent adverse reactions (> 7%) with triple therapy were diarrhea, taste perversion, and headache. (6.1)

To report SUSPECTED ADVERSE REACTIONS, contact Cumberland Pharmaceuticals Inc. at 1-877-484-2700 or FDA at 1-800-FDA-1088 or www.fda.gov/medwatch.

7 DRUG INTERACTIONS

- Antiarrhythmics: Risk of torsades de pointes and other arrhythmias with concurrent use of clarithromycin and quinidine, disopyramide, and digoxin. Monitor ECGs and serum digoxin concentrations. (7.4)
- Oral anticoagulants: Concomitant administration of omeprazole or clarithromycin may potentiate the anticoagulant effects of warfarin and other oral anticoagulants. Monitor prothrombin times and INR. (7.5)
- Atazanavir and nelfinavir: Omeprazole reduces plasma concentrations of atazanavir and nelfinavir. Concomitant use is not recommended. (7.6)
- Saquinavir: Omeprazole increases plasma concentrations of saquinavir. Monitor for toxicity and consider dose reduction of saquinavir. (7.6)
- Cilostazol: Omeprazole increases systemic exposure of cilostazol and one of its active metabolites. Consider dose reduction of cilostazol. (7.7)
- Tacrolimus: Omeprazole may increase serum concentrations of tacrolimus. Frequently monitor whole blood trough concentrations of tacrolimus. (7.8)
- Theophylline: Clarithromycin may increase serum concentrations of theophylline. Monitor serum theophylline concentrations. (7.9)
- Carbamazepine: Clarithromycin may increase plasma concentrations of carbamazepine. Monitor blood concentrations of carbamazepine. (7.10)
- Sildenafil: Clarithromycin may increase systemic exposure of sildenafil. Consider dose reduction of sildenafil. (7.11)
- HMG-CoA reductase inhibitors (statins): Clarithromycin may alter the effect of HMG-CoA reductase inhibitors (statins). (7.12)
- Drugs metabolized by cytochrome P450 (e.g., diazepam, warfarin, phenytoin, cyclosporine, disulfiram, benzodiazepines): Omeprazole can prolong their elimination. Monitor and determine need for dose adjustments. (7, 7.13)
- Probenecid: Probenecid may increase blood concentrations of the amoxicillin. (7.14)
- Omeprazole may interfere with drugs for which gastric pH affects bioavailability (e.g., ketoconazole, iron salts, ampicillin esters, digoxin, and mycophenolate mofetil). (7.15)

8 USE IN SPECIFIC POPULATIONS

- Hepatic Impairment: Avoid use (8.7)
- Asian Patients: Avoid use unless it is deemed that the benefits outweigh the risks. (8.8)

FULL PRESCRIBING INFORMATION

1 INDICATIONS AND USAGE

1.1 Eradication of Helicobacter pylori in Patients with Active Duodenal Ulcer or History of Duodenal Ulcer Disease

OMECLAMOX-PAK (Omeprazole delayed-release capsules, clarithromycin tablets, and amoxicillin capsules taken together) are indicated for the treatment of patients with Helicobacter pylori infection and duodenal ulcer disease (active or one-year history) to eradicate H. pylori in adults. Eradication of H. pylori has been shown to reduce the risk of duodenal ulcer recurrence [see Clinical Studies (14.1)].

1.2 Usage

To reduce the development of drug-resistant bacteria and maintain the effectiveness of OMECLAMOX-PAK and other antibacterial drugs OMECLAMOX-PAK should be used only to treat or prevent infections that are proven or strongly suspected to be caused by susceptible bacteria. When culture and susceptibility information are available, they should be considered in selecting or modifying antibacterial therapy. In the absence of such data, local epidemiology and susceptibility patterns may contribute to the empiric selection of therapy.

2 DOSAGE AND ADMINISTRATION

The recommended adult oral dose and regimen is omeprazole delayed-release capsules 20 mg plus clarithromycin 500 mg plus amoxicillin 1000 mg, each given twice daily, for 10 days, in the morning and evening before eating a meal. Inform patients that omeprazole, clarithromycin, and amoxicillin should not be crushed or chewed, and should be swallowed whole.

In patients with an ulcer present at the time of initiation of therapy, an additional 18 days of omeprazole 20 mg once daily is recommended for ulcer healing and symptom relief.

3 DOSAGE FORMS AND STRENGTHS

OMECLAMOX-PAK is supplied in a carton containing ten individual daily administration cards. Each card contains:

- Omeprazole Delayed-Release Capsules, USP, 20 mg

Two opaque, hard gelatin lavender and grey capsules, with ‘R 158’ and ‘OMEPRAZOLE 20 mg’ imprinted on the capsules in black ink, containing off-white to pale-yellow, elliptical spherical pellets.

- Clarithromycin Tablets, USP, 500 mg

Two white, biconvex beveled-edge capsule-shaped coated tablets debossed with ‘54 312’ on one side and plain on the other side.

- Amoxicillin Capsules, USP, 500 mg

Four opaque hard gelatin yellow capsules, marked ‘GG849’.

4 CONTRAINDICATIONS

4.1 Hypersensitivity

OMECLAMOX-PAK is contraindicated in the following patients:

- Known history of hypersensitivity to omeprazole or benzimidazoles, any macrolide antibacterial drug, or any penicillin. Hypersensitivity reactions to omeprazole may include anaphylaxis, anaphylactic shock, angioedema, bronchospasm, acute tubulointerstitial nephritis, and urticaria. Hypersensitivity reactions to clarithromycin may include anaphylaxis, Stevens-Johnson syndrome, and toxic epidermal necrolysis. Hypersensitivity reactions to amoxicillin may include serum sickness like reactions, erythematous maculopapular rashes, erythema multiforme, Stevens-Johnson syndrome, exfoliative dermatitis, toxic epidermal necrolysis, acute generalized exanthematous pustulosis, hypersensitivity vasculitis and urticaria [see Warnings and Precautions (5.7), Adverse Reactions (6.3)].
- Serious and occasionally fatal hypersensitivity (anaphylactic) reactions have been reported in patients on penicillin therapy. Although anaphylaxis is more frequent following parenteral therapy, it has occurred in patients on oral penicillins. These reactions are more likely to occur in individuals with a history of penicillin hypersensitivity and/or a history of sensitivity to multiple allergens. Before initiating therapy with amoxicillin, careful inquiry should be made concerning previous hypersensitivity reactions to penicillins, cephalosporins or other allergens.

4.2 Serious Drug Interactions

- OMECLAMOX-PAK is contraindicated in patients taking ergotamine or dihydroergotamine and pimozide. Cardiac arrhythmias, some fatal, have been reported with the use of clarithromycin and/or erythromycin and pimozide. Arrhythmias have included QT prolongation, ventricular tachycardia, ventricular fibrillation, and torsades de pointes, and are most likely due to inhibition of metabolism of these drugs by clarithromycin and/or erythromycin [see Drug Interactions (7.2, 7.3)].
- Coadministration of OMECLAMOX-PAK with lurasidone is contraindicated since it may result in an increase in lurasidone expose and the potential for serious adverse reactions [see Drug Interactions (7)].

5 WARNINGS AND PRECAUTIONS

5.1 Embryo-Fetal Toxicity

Clarithromycin, a component of OMECLAMOX-PAK, has demonstrated adverse effects on pregnancy outcomes and/or embryo-fetal development in monkeys, rats, mice, and rabbits at doses that produced plasma concentrations 2 to 17 times the serum concentrations achieved in humans at the maximum recommended human dose.

Based on findings in animal studies, OMECLAMOX-PAK is not recommended for use in pregnant women except in clinical circumstances where no alternative therapy is appropriate. If OMECLAMOX-PAK is used during pregnancy, or if pregnancy occurs while the patient is taking this drug, the patient should be apprised of the potential hazard to the fetus [see Use in Specific Populations (8.1)].

5.2 Severe Cutaneous Adverse Reactions

Severe cutaneous adverse reactions (SCAR), including Stevens-Johnson syndrome (SJS), toxic epidermal necrolysis (TEN), drug reaction with eosinophilia and systemic symptoms (DRESS), and acute generalized exanthematous pustulosis (AGEP) have been reported with the components of OMECLAMOX-PAK: omeprazole, clarithromycin, and amoxicillin [see Adverse Reactions (6.3)].

Discontinue OMECLAMOX-PAK at the first signs or symptoms of SCAR or other signs of hypersensitivity and consider further evaluation.

5.3 Colchicine Toxicity with Clarithromycin

There have been postmarketing reports of colchicine toxicity, some fatal, with concomitant use of clarithromycin and colchicine, especially in the elderly, some of which occurred in patients with renal insufficiency. Monitor patients for clinical symptoms of colchicine toxicity [see Drug Interactions (7.1)].

5.4 Myasthenia Gravis

Exacerbation of symptoms of myasthenia gravis and new onset of symptoms of myasthenic syndrome have been reported in patients receiving clarithromycin therapy. Monitor patients for symptoms.

5.5 Clostridioides difficile-associated diarrhea

Clostridioides difficile-associated diarrhea (CDAD) has been reported with use of clarithromycin and amoxicillin, and may range in severity from mild diarrhea to fatal colitis [see Adverse Reactions (6.3)]. Treatment with antibacterial agents alters the normal flora of the colon leading to overgrowth of C. difficile.

C. difficile produces toxins A and B which contribute to the development of CDAD. Hypertoxin-producing strains of C. difficile cause increased morbidity and mortality, as these infections can be refractory to antimicrobial therapy and may require colectomy. CDAD must be considered in all patients who present with diarrhea following antibiotic use. Careful medical history is necessary since CDAD has been reported to occur over two months after the administration of antibacterial agents.

If CDAD is suspected or confirmed, ongoing antibiotic use not directed against C. difficile may need to be discontinued. Appropriate fluid and electrolyte management, protein supplementation, antibiotic treatment of C. difficile, and surgical evaluation should be instituted as clinically indicated.

5.6 Concomitant Gastric Malignancy

Symptomatic response to therapy with omeprazole does not preclude the presence of gastric malignancy.

5.7 AcuteTubulointerstitial Nephritis

Acute tubulointerstitial nephritis (TIN) has been observed in patients taking PPIs including omeprazole, a component of OMECLAMOX-PAK. TIN may occur at any point during PPI therapy. Patients may present with varying signs and symptoms from symptomatic hypersensitivity reactions, to non-specific symptoms of decreased renal function (e.g., malaise, nausea, anorexia). In reported case series, some patients were diagnosed on biopsy and in the absence of extra-renal manifestations (e.g., fever, rash or arthralgia). Discontinue OMECLAMOX-PAK and evaluate patients with suspected acute TIN [see Contraindications (4.1)].

5.8 Cutaneous and Systemic Lupus

Cutaneous lupus erythematosus (CLE) and systemic lupus erythematosus (SLE) have been reported in patients taking PPIs, including omeprazole. These events have occurred as both new onset and an exacerbation of existing autoimmune disease. The majority of PPI-induced lupus erythematosus cases were CLE.

The most common form of CLE reported in patients treated with PPIs was subacute CLE (SCLE) and occurred within weeks to years after continuous drug therapy in patients ranging from infants to the elderly. Generally, histological findings were observed without organ involvement.

Systemic lupus erythematosus (SLE) is less commonly reported than CLE in patients receiving PPIs. PPI associated SLE is usually milder than non-drug induced SLE. Onset of SLE typically occurred within days to years after initiating treatment primarily in patients ranging from young adults to the elderly. The majority of patients presented with rash; however, arthralgia and cytopenia were also reported.

Avoid administration of PPIs for longer than medically indicated. If signs or symptoms consistent with CLE or SLE are noted in patients receiving OMECLAMOX-PAK, discontinue the drug and refer the patient to the appropriate specialist for evaluation. Most patients improve with discontinuation of the PPI alone in 4 to 12 weeks. Serological testing (e.g. ANA) may be positive and elevated serological test results may take longer to resolve than clinical manifestations.

5.9 Development of Bacterial Superinfections

The possibility of superinfections with mycotic or bacterial pathogens should be kept in mind during therapy with OMECLAMOX-PAK due to the clarithromycin and amoxicillin components. If superinfections occur, OMECLAMOX-PAK should be discontinued and appropriate therapy instituted.

5.10 Mononucleosis and Ampicillin

A high percentage of patients with mononucleosis who receive ampicillin develop an erythematosus skin rash. Thus, administration of ampicillin-class antibiotics is not recommended in patients with mononucleosis.

5.11 Development of Drug Resistant Bacteria

Prescribing OMECLAMOX-PAK (clarithromycin or amoxicillin component) in the absence of a proven or strongly suspected bacterial infection or a prophylactic indication is unlikely to provide benefit to the patient and increases the risk of the development of drug-resistant bacteria.

6 ADVERSE REACTIONS

The following serious adverse reactions are described elsewhere in the labeling:

- Hypersensitivity [see Contraindications (4.1)]
- Myasthenia Gravis [see Warnings and Precautions (5.4)]
- Clostridioides difficile-associated diarrhea [see Warnings and Precautions (5.5)]
- Acute Tubulointerstitial Nephritis [see Warnings and Precautions (5.7)]

6.1 Clinical Trials Experience

Because clinical trials are conducted under widely varying conditions, adverse reaction rates observed in the clinical trials of a drug cannot be directly compared to rates in the clinical trials of another drug and may not reflect the rates observed in practice.

In clinical trials using triple therapy with omeprazole, clarithromycin, and amoxicillin, no adverse reactions unique to triple therapy were observed. Adverse reactions observed were limited to those previously reported with omeprazole, clarithromycin, or amoxicillin alone. The most frequent adverse reactions observed in clinical trials using combination therapy with omeprazole, clarithromycin, and amoxicillin (n = 274) were diarrhea (14%), taste perversion (10%), and headache (7%). None of these occurred at a higher frequency than that reported by patients taking antimicrobial agents alone.

6.2 Adverse Reactions from Labeling for the Individual Components of OMECLAMOX-PAK

The safety data below reflect exposure to omeprazole delayed-release capsules and clarithromycin worldwide in clinical trials for various indications using doses and durations of therapy that may differ from how they are used as a component of OMECLAMOX-PAK. For complete information on these reactions, see the full prescribing information for omeprazole delayed-release capsules and clarithromycin.

Omeprazole:

The most common adverse reactions reported (i.e., with an incidence rate ≥ 2%) in 3096 patients from omeprazole delayed-release capsules-treated patients enrolled in clinical trials included headache (6.9%), abdominal pain (5.2%), nausea (4.0%), diarrhea (3.7%), vomiting (3.2%), and flatulence (2.7%).

Additional adverse reactions that were reported with an incidence rate ≥ 1% included acid regurgitation (1.9%), upper respiratory infection (1.9%), constipation (1.5%), dizziness (1.5%), rash (1.5%), asthenia (1.3%), back pain (1.1%), and cough (1.1%).

The clinical trial safety profile in patients greater than 65 years of age was similar to that in patients 65 years of age or less.

Clarithromycin:

The most frequently reported events in adults were diarrhea (3%), nausea (3%), abnormal taste (3%), dyspepsia (2%), abdominal pain/discomfort (2%), and headache (2%). Most of these events were described as mild or moderate in severity. Of the reported adverse events, only 1% were described as severe. Fewer than 3% of adult patients without mycobacterial infections discontinued therapy because of drug-related side effects.

6.3 Post-Marketing Experience with the Individual Components of OMECLAMOX-PAK

Because these reactions are voluntarily reported from a population of uncertain size, it is not always possible to reliably estimate their actual frequency or establish a causal relationship to drug exposure.

Omeprazole:

Body As a Whole: Hypersensitivity reactions including anaphylaxis, anaphylactic shock, angioedema, bronchospasm, interstitial nephritis, urticaria, (see also Skin below); fever; pain; fatigue; malaise.

Cardiovascular: Chest pain or angina, tachycardia, bradycardia, palpitations, elevated blood pressure, peripheral edema.

Endocrine: Gynecomastia.

Gastrointestinal: Pancreatitis (some fatal), anorexia, irritable colon, fecal discoloration, esophageal candidiasis, mucosal atrophy of the tongue, stomatitis, abdominal swelling, dry mouth. During treatment with omeprazole, gastric fundic gland polyps have been noted rarely. These polyps are benign and appear to be reversible when treatment is discontinued. Gastroduodenal carcinoids have been reported in patients with Zollinger-Ellison syndrome on long-term treatment with omeprazole. This finding is believed to be a manifestation of the underlying condition, which is known to be associated with such tumors.

Hepatic: Liver disease including hepatic failure (some fatal), liver necrosis (some fatal), hepatic encephalopathy hepatocellular disease, cholestatic disease, mixed hepatitis, jaundice, and elevations of liver function tests [ALT, AST, GGT, alkaline phosphatase, and bilirubin].

Metabolic/Nutritional: Hypoglycemia, hypomagnesemia with or without hypocalcemia and/or hypokalemia, hyponatremia, weight gain.

Musculoskeletal: Muscle weakness, myalgia, muscle cramps, joint pain, leg pain.

Nervous System/Psychiatric: Psychiatric and sleep disturbances including depression, agitation, aggression, hallucinations, confusion, insomnia, nervousness, apathy, somnolence, anxiety, and dream abnormalities; tremors, paresthesia; vertigo.

Respiratory: Epistaxis, pharyngeal pain.

Skin: SCAR, including TEN (some fatal), SJS, DRESS, and AGEP; erythema multiforme; photosensitivity; urticaria; rash; skin inflammation; pruritus; petechiae; purpura; alopecia; dry skin; hyperhidrosis.

Special Senses: Tinnitus, taste perversion.

Ocular: Optic atrophy, anterior ischemic optic neuropathy, optic neuritis, dry eye syndrome, ocular irritation, blurred vision, double vision.

Urogenital: Interstitial nephritis, hematuria, proteinuria, elevated serum creatinine, microscopic pyuria, urinary tract infection, glycosuria, urinary frequency, testicular pain, erectile dysfunction.

Hematologic: Agranulocytosis (some fatal), hemolytic anemia, pancytopenia, neutropenia, anemia, thrombocytopenia, leukopenia, leukocytosis.

Clarithromycin:

Hypersensitivity Reactions: Allergic reactions ranging from urticaria and mild skin eruptions to rare cases of anaphylaxis have occurred.

Gastrointestinal: Glossitis, stomatitis, oral moniliasis, anorexia, vomiting, pancreatitis, tongue discoloration.

Hematologic: Thrombocytopenia, leukopenia, neutropenia.

Other: There have been reports of tooth discoloration in patients treated with clarithromycin. Tooth discoloration is usually reversible with professional dental cleaning.

Nervous System/Psychiatric: There have been isolated reports of hearing loss, which is usually reversible, occurring chiefly in elderly women. Reports of alterations of the sense of smell, usually in conjunction with taste perversion or taste loss have also been reported.

Transient CNS events including anxiety, behavioral changes, confusional states, convulsions, depersonalization, disorientation, hallucinations, insomnia, manic behavior, nightmares, psychosis, tinnitus, tremor, dizziness and vertigo have been reported during postmarketing surveillance. Events usually resolve with discontinuation of the drug.

Hepatic: Hepatic dysfunction, including increased liver enzymes, and hepatocellular and/or cholestatic hepatitis, with or without jaundice, has been infrequently reported with clarithromycin. This hepatic dysfunction may be severe and is usually reversible. In very rare instances, hepatic failure with fatal outcome has been reported and generally has been associated with serious underlying diseases and/or concomitant medications.

Metabolic: There have been rare reports of hypoglycemia, some of which have occurred in patients taking oral hypoglycemic agents or insulin.

Cardiac: As with other macrolides, clarithromycin has been associated with QT prolongation and ventricular arrhythmias, including ventricular tachycardia and torsades de pointes.

Renal: There have been reports of interstitial nephritis coincident with clarithromycin use.

Skin: SCAR, including TEN, SJS, DRESS, and AGEP.

Amoxicillin:

Gastrointestinal: Nausea, vomiting, diarrhea, anorexia, gastritis, black hairy tongue, glossitis, stomatitis, and hemorrhagic/C.difficile-associated colitis. [see Warnings and Precautions (5.5)].

Hypersensitivity Reactions: Serum sickness like reactions, erythematous maculopapular rashes, erythema multiforme, exfoliative dermatitis, hypersensitivity vasculitis and urticaria have been reported. Reactions are more likely to occur in individuals who have previously demonstrated hypersensitivity to penicillins and in those with a history of allergy, asthma, hay fever, or urticaria.

Hepatic: A moderate rise in AST (SGOT) and/or ALT (SGPT) has been noted, but the significance of this finding is unknown. Hepatic dysfunction including cholestatic jaundice, hepatic cholestasis and acute cytolytic hepatitis have been reported.

Renal: Crystalluria has also been reported [see Overdosage (10)].

Hemic and Lymphatic Systems: Anemia, including hemolytic anemia, thrombocytopenia, thrombocytopenic purpura, eosinophilia, leukopenia and agranulocytosis have been reported during therapy with penicillins. These reactions are usually reversible on discontinuation of therapy and are believed to be hypersensitivity phenomena.

Nervous System/Psychiatric: Reversible hyperactivity, agitation, anxiety, insomnia, confusion, aseptic meningitis, behavioral changes, and/or dizziness have been reported rarely.

Miscellaneous: Tooth discoloration (brown, yellow, or gray staining) has been rarely reported. Most reports occurred in pediatric patients. Discoloration was reduced or eliminated with brushing or dental cleaning in most cases.

Skin: SCAR, including TEN, SJS, DRESS, and AGEP.

Changes in Laboratory Values: Changes in laboratory values with possible clinical significance were as follows: Hepatic – elevated SGPT (ALT) less than 1%, SGOT (AST) less than 1%, GGT less than 1%, alkaline phosphatase less than 1%, LDH less than 1%, total bilirubin less than 1%; Hematologic – decreased WBC less than 1%, elevated prothrombin time 1%; Renal – elevated BUN 4%, elevated serum creatinine less than 1%. GGT, alkaline phosphatase, and prothrombin time data are from adult studies only.

7 DRUG INTERACTIONS

Effect of Omeprazole

Omeprazole is a substrate and an inhibitor of CYP2C19 in vivo, a substrate of CYP3A4 in vivo, and an inhibitor of CYP2C19 in vitro. Therefore, omeprazole may affect the metabolism and plasma concentrations of drugs that are metabolized by these CYP enzymes. Although in healthy subjects no interaction with theophylline or propranolol was reported, there have been reports of an interaction with other drugs metabolized via the CYP enzyme system (e.g., cyclosporine, disulfiram, benzodiazepines). Carefully monitor patients taking these drugs to determine if dosage adjustments of these drugs are necessary when taken concomitantly with omeprazole.

Effect of Clarithromycin

Clarithromycin is a substrate and inhibitor of CYP3A enzymes. Coadministration of clarithromycin with drugs metabolized by CYP3A may be associated with elevations in drug concentrations that could increase the therapeutic and adverse effects of the concomitant drug. There have been reports of CYP3A-based interactions of erythromycin and/or clarithromycin with cyclosporine, tacrolimus, alfentanil, rifabutin, methylprednisolone, cilostazol, bromocriptine and lurasidone. OMECLAMOX_PAK is contraindicated in patients receiving lurasidone [see Contraindications (4.2)]. In addition, there have been reports of interactions of erythromycin or clarithromycin with drugs not thought to be metabolized by CYP3A, including: hexobarbital, phenytoin, and valproate.

7.1 Colchicine

Concurrent use of colchicine and OMECLAMOX-PAK may increase plasma colchicine concentrations. Colchicine is a substrate for both CYP3A and the efflux transporter, P-glycoprotein (Pgp). The clarithromycin component of OMECLAMOX-PAK is known to inhibit CYP3A and Pgp. When clarithromycin and colchicine are administered together, inhibition of Pgp and/or CYP3A by clarithromycin may lead to increased plasma exposure to colchicine. Monitor patients for clinical symptoms of colchicine toxicity [see Warnings and Precautions (5.3)].

7.2 Ergotamine/Dihydroergotamine

Ergotamine/dihydroergotamine plasma concentrations may increase when administered concomitantly with OMECLAMOX-PAK. Post-marketing reports indicate that coadministration of clarithromycin with ergotamine or dihydroergotamine has been associated with acute ergot toxicity characterized by vasospasm and ischemia of the extremities and other tissues including the central nervous system. Concomitant administration of clarithromycin with ergotamine or dihydroergotamine is contraindicated [see Contraindications (4.2)].

7.3 Pimozide

The coadministration of pimozide and OMECLAMOX-PAK may increase the pimozide plasma concentrations due to an interaction with the clarithromycin component of OMECLAMOX-PAK. Post-marketing reports indicate that coadministration of clarithromycin with pimozide has been associated with cardiac arrhythmias (QT prolongation, ventricular tachycardia, ventricular fibrillation, and torsades de pointes). Two sudden deaths have been reported when clarithromycin was added to ongoing pimozide therapy. Pimozide is metabolized partly by CYP3A4. When clarithromycin and pimozide are administered together, inhibition of CYP3A4 by clarithromycin may lead to increased plasma exposure to pimozide. OMECLAMOX-PAK is contraindicated in patients receiving pimozide [see Contraindications (4.2)].

7.4 Antiarrhythmics

Concurrent use of antiarrhythmic drugs and OMECLAMOX-PAK may potentiate the antiarrhythmic effects due to an interaction with the clarithromycin component of OMECLAMOX-PAK. There have been post-marketing reports of torsades de pointes occurring with concurrent use of clarithromycin and quinidine or disopyramide. Elevated digoxin serum concentrations in patients receiving clarithromycin and digoxin concomitantly have also been reported in post-marketing surveillance. Some patients have shown clinical signs consistent with digoxin toxicity, including potentially fatal arrhythmias. Monitor electrocardiograms for QTc prolongation during coadministration of OMECLAMOX-PAK with antiarrhythmic drugs. Serum concentrations of antiarrhythmics, including digoxin, should also be monitored.

7.5 Anticoagulants

The simultaneous administration of anticoagulants and OMECLAMOX-PAK may alter the anticoagulant effects of warfarin and other oral anticoagulants due to an interaction with the omeprazole and clarithromycin components of OMECLAMOX-PAK. Monitor prothrombin time and INR in patients receiving OMECLAMOX-PAK and oral anticoagulants simultaneously.

There have been reports of increased INR and prothrombin time in patients receiving proton pump inhibitors, including omeprazole, and warfarin concomitantly. Increases in INR and prothrombin time may lead to abnormal bleeding and even death.

Spontaneous reports in the post-marketing period suggest that concomitant administration of clarithromycin and oral anticoagulants may potentiate the effects of the oral anticoagulants.

7.6 Antiretroviral Drugs

Concurrent use of antiretroviral agents and OMECLAMOX-PAK may alter the antiretroviral effects due to interactions with the omeprazole or clarithromycin components of OMECLAMOX-PAK. Omeprazole has been reported to interact with some antiretroviral drugs such as atazanavir, nelfinavir, and saquinavir.

Concomitant use of atazanavir or nelfinavir with omeprazole is not recommended unless the benefits of taking atazanavir or nelfinavir with OMECLAMOX-PAK outweigh the risks. Coadministration of atazanavir or nelfinavir with proton pump inhibitors is expected to substantially decrease atazanavir or nelfinavir plasma concentrations and thereby reduce the therapeutic effect of either of these drugs [see Clinical Pharmacology (12.3)].

Coadministration of saquinavir with omeprazole may increase the serum concentrations of saquinavir. Dose reduction of saquinavir should be considered when coadministered with OMECLAMOX-PAK [see Clinical Pharmacology (12.3)].

7.7 Cilostazol

Concomitant administration of OMECLAMOX-PAK and cilostazol may increase systemic exposure of cilostazol due to an interaction with the omeprazole component of OMECLAMOX-PAK. Therefore, a dose reduction of cilostazol by 50% should be considered when concomitantly administered with OMECLAMOX-PAK [see Clinical Pharmacology (12.3)].

7.8 Tacrolimus

Concomitant administration of OMECLAMOX-PAK and tacrolimus may increase the serum concentrations of tacrolimus due to an interaction with the omeprazole component of OMECLAMOX-PAK. Frequent monitoring of whole blood trough concentrations of tacrolimus is recommended when concomitantly administered with OMECLAMOX-PAK.

7.9 Theophylline

OMECLAMOX-PAK use in patients who are receiving theophylline may be associated with an increase of serum theophylline concentrations due to an interaction with the clarithromycin component of OMECLAMOX-PAK. Monitoring of serum theophylline concentrations should be considered for patients receiving high doses of theophylline or with baseline concentrations in the upper therapeutic range [see Clinical Pharmacology (12.3)].

7.10 Carbamazepine

The simultaneous administration of carbamazepine and OMECLAMOX-PAK may alter the effect of carbamazepine due to an interaction with the clarithromycin component of OMECLAMOX-PAK. Concomitant administration of single doses of clarithromycin and carbamazepine has been shown to result in increased plasma concentrations of carbamazepine. Blood level monitoring of carbamazepine should be considered when administered concomitantly with OMECLAMOX-PAK.

7.11 Sildenafil

The systemic exposure of sildenafil may increase when it is administered concomitantly with OMECLAMOX-PAK due to an interaction with the clarithromycin component of OMECLAMOX-PAK; consider a reduction in sildenafil dosage (see sildenafil full prescribing information).

7.12 HMG-CoA Reductase Inhibitors (Statins)

Concurrent use of HMG-CoA reductase inhibitors (statins) and OMECLAMOX-PAK may alter the effect of HMG-CoA due to an interaction with the clarithromycin component of OMECLAMOX-PAK. As with other macrolides, clarithromycin has been reported to increase concentrations of statins (e.g., lovastatin and simvastatin). Rare reports of rhabdomyolysis have been reported in patients taking these drugs concomitantly.

7.13 Triazolobenzodiazepines (e.g., triazolam and alprazolam) and related Benzodiazepines (e.g., midazolam)

The effect of triazolobenzodiazepines/related benzodiazepines may be altered when administered concomitantly with OMECLAMOX-PAK due to an interaction with the clarithromycin component. There have been postmarketing reports of drug interactions and CNS effects (e.g., somnolence and confusion) with the concomitant use of clarithromycin and triazolam.

7.14 Probenecid

Probenecid decreases the renal tubular secretion of amoxicillin. Concurrent use of OMECLAMOX-PAK and probenecid may result in increased and prolonged blood concentrations of the amoxicillin component of OMECLAMOX-PAK.

7.15 Drugs for which Gastric pH can affect Bioavailability

Due to its effects on gastric acid secretion, omeprazole can reduce the absorption of drugs where gastric pH is an important determinant of their bioavailability. As with other drugs that decrease the intragastric acidity, the absorption of drugs such as ketoconazole, atazanavir, iron salts, erlotinib, and mycophenolate mofetil can decrease, while the absorption of drugs such as digoxin can increase during treatment with omeprazole.

Concomitant treatment with omeprazole (20 mg daily) and digoxin in healthy subjects increased the bioavailability of digoxin by 10% (30% in two subjects). Coadministration of digoxin with omeprazole is expected to increase the systemic exposure of digoxin. Therefore, patients may need to be monitored when digoxin is taken concomitantly with omeprazole.

Coadministration of omeprazole in healthy subjects and in transplant patients receiving mycophenolate mofetil has been reported to reduce the exposure to mycophenolic acid (MPA), the active moiety, possibly due to a decrease in MPA solubility at an increased gastric pH. The clinical relevance of reduced MPA exposure on organ rejection has not been established in transplant patients receiving proton pump inhibitors (PPIs) and mycophenolate mofetil. Use omeprazole with caution in transplant patients receiving mycophenolate mofetil [see Clinical Pharmacology (12.3)].

7.16 Drug-Laboratory Test Interactions

High urine concentrations of ampicillin may result in false-positive reactions when testing for the presence of glucose in urine using glucose tests based on the Benedict's copper reduction reaction that determines the amount of reducing substances like glucose in urine. Since this effect may also occur with amoxicillin, it is recommended that glucose tests based on enzymatic glucose oxidase reactions be used.

Following administration of ampicillin to pregnant women, a transient decrease in plasma concentration of total conjugated estradiol, estriol-glucuronide, conjugated estrone, and estradiol has been noted. This effect may also occur with amoxicillin.

8 USE IN SPECIFIC POPULATIONS

8.1 Pregnancy

Risk Summary

Based on findings in animal studies for omeprazole and clarithromycin (components of OMECLAMOX-PAK), use of OMECLAMOX-PAK during pregnancy may cause fetal harm. OMECLAMOX-PAK is not recommended for use in pregnant women except in clinical circumstances where no alternative therapy is appropriate. If OMECLAMOX-PAK is used during pregnancy, or if pregnancy occurs while taking OMECLAMOX-PAK, the patient should be apprised of the potential hazard to the fetus [see Warnings and Precautions (5.1)]. There are no adequate and well controlled studies of omeprazole, clarithromycin, or amoxicillin (used separately or together) in pregnant women. Clarithromycin demonstrated adverse developmental effects in four animal species at clinically relevant doses. Omeprazole increased embryo-fetal loss in rabbits, but animal studies and multiple human studies do not show an increased risk for major malformations. There was no evidence of harm to the fetus in mice and rats due to amoxicillin.

Omeprazole

There are no adequate and well-controlled studies with omeprazole in pregnant women. Available epidemiologic data fail to demonstrate an increased risk of major congenital malformations or other adverse pregnancy outcomes with first trimester omeprazole use. Reproduction studies in rats and rabbits resulted in dose-dependent embryo-lethality at omeprazole doses that were approximately 3.4 to 34 times an oral human dose of 40 mg.

No fetal malformations were observed in animal reproduction studies with administration of oral esomeprazole (an enantiomer of omeprazole) magnesium in rats and rabbits during organogenesis with doses about 68 times and 42 times, respectively, an oral human dose of 40 mg esomeprazole or 40 mg omeprazole. Changes in bone morphology were observed in offspring of rats dosed through most of pregnancy and lactation at doses equal to or greater than approximately 34 times the clinical dose of omeprazole. When maternal administration was confined to gestation only, there were no effects on bone physeal morphology in the offspring at any age [see Data].

Clarithromycin

Limited data from a small number of published human studies with clarithromycin use during pregnancy are insufficient to inform drug-associated risks of major birth defects, miscarriage, or adverse maternal or fetal outcomes. In animal reproduction studies, administration of oral clarithromycin to pregnant mice, rats, rabbits, and monkeys during the period of organogenesis produced malformations in rats (cardio-vascular anomalies) and mice (cleft palate) at clinically relevant doses based on body surface area comparison. Fetal effects in mice, rats, and monkeys (e.g., reduced fetal survival, body weight, body weight gain) and implantation losses in rabbits were generally considered to be secondary to maternal toxicity (see Animal Data).

Amoxicillin

Available data from published epidemiologic studies and pharmacovigilance case reports over several decades with amoxicillin use have not established drug-associated risks of major birth defects, miscarriage, or adverse maternal or fetal outcomes (see Data). No adverse developmental effects were observed in animal reproduction studies with administration of amoxicillin to pregnant mice and rats at doses up to 3 and 6 times the recommended human dose (see Data).

The estimated background risk of major birth defects and miscarriage for the indicated population is unknown. All pregnancies have a background risk of birth defect, loss, or other adverse outcomes. In the U.S. general population, the estimated background risk of major birth defects and miscarriage in clinically recognized pregnancies is 2 to 4% and 15 to 20%, respectively.

Data

Animal Data

Omeprazole

Reproductive studies conducted with omeprazole in rats at oral doses up to 138 mg/kg/day (about 34 times an oral human dose of 40 mg based on body surface area comparison) and in rabbits at doses up to 69.1 mg/kg/day (about 34 times an oral human dose of 40 mg) during organogenesis did not disclose any evidence for a teratogenic potential of omeprazole. In rabbits, omeprazole in a dose range of 6.9 to 69.1 mg/kg/day (about 3.4 to 34 times an oral human dose of 40 mg) administered during organogenesis produced dose-related increases in embryo-lethality, fetal resorptions, and pregnancy disruptions. In rats, dose-related embryo/fetal toxicity and postnatal developmental toxicity were observed in offspring resulting from parents treated with omeprazole at 13.8 to 138.0 mg/kg/day (about 3.4 to 34 times an oral human doses of 40 mg), administered prior to mating through the lactation period.

Clarithromycin

Animal reproduction studies were conducted in mice, rats, rabbits, and monkeys with oral and intravenously administered clarithromycin. In pregnant mice, clarithromycin was administered during organogenesis (gestation day [GD] 6 to 15) at oral doses of 15, 60, 250, 500, or 1000 mg/kg/day. Reduced body weight observed in dams at 1000 mg/kg/day (3 times the maximum recommended human dose [MRHD]) resulted in reduced survival and body weight of the fetuses. At ≥ 500 mg/kg/day, increases in the incidence of post-implantation loss and cleft palate in the fetuses were observed. No adverse developmental effects were observed in mice at ≤ 250 mg/kg/day (≤ 1 times MRHD comparison).

In pregnant Sprague Dawley rats, clarithromycin administered during organogenesis (GD 6 to 15) at oral doses of 15, 50, or 150 mg/kg/day resulted in reduced body weight and food consumption in dams at 150 mg/kg/day. Reductions in body weight and food consumption was observed in dams at 150 mg/kg/day. Increased resorptions and reduced body weight of the fetuses at this dose were considered secondary to maternal toxicity. Additionally, at 150 mg/kg/day (1 times MRHD), a low incidence of cardiovascular anomalies (complete situs inversus, undivided truncus, IV septal defect) was observed in the fetuses. Clarithromycin did not cause adverse developmental effects in rats at 50 mg/kg/day (0.3 times MRHD comparison). Intravenous dosing of clarithromycin during organogenesis in rats (GD 6 to 15) at 15, 50, or 160 mg/kg/day was associated with maternal toxicity (reduced body weight, body-weight gain, and food consumption) at 160 mg/kg/day but no evidence of adverse developmental effects at any dose (≤ 1 times MRHD comparison).

In pregnant Wistar rat, clarithromycin was administered during organogenesis (GD 7 to 17) at oral doses of 10, 40, or 160 mg/kg/day. Reduced body weight and food consumption were observed in dams at 160 mg/kg/day but there was no evidence of adverse developmental effects at any dose (≤ 1 times MRHD comparison).

In pregnant rabbits, clarithromycin administered during organogenesis (GD 6 to 18) at oral doses of 10, 35, or 125 mg/kg/day resulted in reduced maternal food consumption and decreased body weight at the highest dose, with no evidence of any adverse developmental effects at any dose (≤ 2 times MRHD comparison). Intravenously administered clarithromycin to pregnant rabbits during organogenesis (GD 6 to 18) in rabbits at 20, 40, 80, or 160 mg/kg/day (≥ 0.3 times MRHD comparison) resulted in maternal toxicity and implantation losses at all doses.

In pregnant monkeys, clarithromycin administered (GD 20 to 50) at oral doses of 35 or 70 mg/kg/day resulted in dose-dependent emesis, poor appetite, fecal changes, and reduced body weight in dams at all doses (≥ 0.5 times MRHD comparison). Growth retardation in 1 fetus at 70 mg/kg/day was considered secondary to maternal toxicity. There was no evidence of primary drug related adverse developmental effects at any dose tested.

In a reproductive toxicology study in rats administered oral clarithromycin late in gestation through lactation (GD 17 to post-natal day 21) at doses of 10, 40, or 160 mg/kg/day (≤ 1 times MRHD comparison), reductions in maternal body weight and food consumption were observed at 160 mg/kg/day. Reduced body-weight gain observed in offspring at 160 mg/kg/day was considered secondary to maternal toxicity. No adverse developmental effects were observed with clarithromycin at any dose tested.

Amoxicillin

Reproduction studies have been performed in mice and rats at doses up to 2000 mg/kg (3 and 6 times the 3 g human dose based on a body surface area comparison and have revealed no evidence of harm to the fetus due to amoxicillin.

Human Data

Omeprazole

Four published epidemiological studies compared the frequency of congenital abnormalities among infants born to women who used omeprazole during pregnancy with the frequency of abnormalities among infants of women exposed to H2-receptor antagonists or other controls.

A population-based retrospective cohort epidemiological study from the Swedish Medical Birth Registry, covering approximately 99% of pregnancies, from 1995 to 99, reported on 955 infants (824 exposed during the first trimester with 39 of these exposed beyond first trimester, and 131 exposed after the first trimester) whose mothers used omeprazole during pregnancy. The number of infants exposed in utero to omeprazole that had any malformation, low birth weight, low Apgar score, or hospitalization was similar to the number observed in this population. The number of infants born with ventricular septal defects and the number of stillborn infants was slightly higher in the omeprazole-exposed infants than the expected number in this population.

A population-based retrospective cohort study covering all live births in Denmark from 1996 to 2009, reported on 1,800 live births whose mothers used omeprazole during the first trimester of pregnancy and 837,317 live births whose mothers did not use any proton pump inhibitor. The overall rate of birth defects in infants born to mothers with first trimester exposure to omeprazole was 2.9% and 2.6% in infants born to mothers not exposed to any proton pump inhibitor during the first trimester.

A retrospective cohort study reported on 689 pregnant women exposed to either H2-blockers or omeprazole in the first trimester (134 exposed to omeprazole) and 1,572 pregnant women unexposed to either during the first trimester. The overall malformation rate in offspring born to mothers with first trimester exposure to omeprazole, an H2-blocker, or were unexposed was 3.6%, 5.5%, and 4.1% respectively.

A small prospective observational cohort study followed 113 women exposed to omeprazole during pregnancy (89% with first trimester exposures). The reported rate of major congenital malformations was 4% in the omeprazole group, 2% in controls exposed to non-teratogens, and 2.8% in disease-paired controls. Rates of spontaneous and elective abortions, preterm deliveries, gestational age at delivery, and mean birth weight were similar among the groups.

Several studies have reported no apparent adverse short-term effects on the infant when single dose oral or intravenous omeprazole was administered to over 200 pregnant women as premedication for cesarean section under general anesthesia.

Amoxicillin

While available studies cannot definitively establish the absence of risk, published epidemiological data and post-marketing case reports have not reported a consistent association with amoxicillin and major birth defects, miscarriage, or adverse maternal or fetal outcomes when amoxicillin was used during pregnancy. Available studies have methodologic limitations, including small sample size, retrospective data collection, under-capture of non-live births, exposure misclassification and inconsistent comparator groups.

8.2 Lactation

Risk Summary

Based on limited human data, clarithromycin and its active metabolite 14-OH clarithromycin are present in human milk at less than 2% of the maternal weight-adjusted dose (see Data). In a separate observational study, reported adverse effects on breast-fed children (rash, diarrhea, loss of appetite, somnolence) were comparable to amoxicillin (see Data). No data are available to assess the effects of clarithromycin or 14-OH clarithromycin on milk production.

Limited data from a single case report suggest omeprazole may be present in human milk. There are no clinical data on the effects of omeprazole on the breastfed infant or on milk production.

Data from a published clinical lactation study indicate that amoxicillin is present in human milk. Published adverse effects with amoxicillin exposure in the breast-fed infant include diarrhea. There are no data on the effects of amoxicillin on milk production.

The development and health benefits of breastfeeding should be considered along with the mother's clinical need for omeprazole or clarithromycin or amoxicillin and any potential adverse effects on the breast-fed child from clarithromycin or from the underlying maternal condition.

Data

Clarithromycin

Serum and milk samples were obtained after 3 days of treatment, at steady state, from one published study of 12 lactating women who were taking clarithromycin 250 mg orally twice daily. Based on the limited data from this study, and assuming milk consumption of 150 mL/kg/day, an exclusively human milk fed infant would receive an estimated average of 136 mcg/kg/day of clarithromycin and its active metabolite, with this maternal dosage regimen. This is less than 2% of the maternal weight-adjusted dose (7.8 mg/kg/day, based on the average maternal weight of 64 kg), and less than 1% of the pediatric dose (15 mg/kg/day) for children greater than 6 months of age.

A prospective observational study of 55 breastfed infants of mothers taking a macrolide antibacterial (6 were exposed to clarithromycin) were compared to 36 breastfed infants of mothers taking amoxicillin. Adverse reactions were comparable in both groups. Adverse reactions occurred in 12.7% of infants exposed to macrolides and included rash, diarrhea, loss of appetite, and somnolence.

Amoxicillin

Penicillins are excreted in human milk. Data from a published clinical lactation study indicates that amoxicillin produces low levels in human milk. Published adverse effects with amoxicillin exposure in the breastfed infant include diarrhea and rash.

8.3 Females and Males of Reproductive Potential

Infertility

Clarithromycin

Administration of clarithromycin resulted in testicular atrophy in rats, dogs and monkeys [see Nonclinical Toxicology (13.1)].

8.4 Pediatric Use

The safety and effectiveness of OMECLAMOX-PAK for pediatric patients with H. pylori have not been established.

8.5 Geriatric Use

Omeprazole

Omeprazole was administered to over 2000 elderly individuals (≥ 65 years of age) in clinical trials in the U.S. and Europe. There were no differences in safety and effectiveness between the elderly and younger subjects. Other reported clinical experience has not identified differences in response between the elderly and younger subjects, but greater sensitivity of some older individuals cannot be ruled out.

Pharmacokinetic studies have shown the elimination rate was somewhat decreased in the elderly and bioavailability was increased. The plasma clearance of omeprazole was 250 mL/min (about half that of young volunteers) and its plasma half-life averaged one hour, about twice that of young healthy volunteers. However, no dosage adjustment is necessary in the elderly [see Clinical Pharmacology (12.3)].

Clarithromycin

In a steady-state study in which healthy elderly subjects (age 65 to 81 years old) were given 500 mg every 12 hours, the maximum serum concentrations and area under the curves of clarithromycin and 14-OH clarithromycin were increased compared to those achieved in healthy young adults. These changes in pharmacokinetics parallel known age-related decreases in renal function. In clinical trials, elderly patients did not have an increased incidence of adverse events when compared to younger patients.

Amoxicillin

An analysis of clinical studies of amoxicillin was conducted to determine whether subjects aged 65 and over respond differently from younger subjects. Of the 1811 subjects treated with amoxicillin, 85% were < 60 years old, 15% were ≥ 61 years old and 7% were ≥ 71 years old. This analysis and other reported clinical experience have not identified differences in responses between the elderly and younger patients, but a greater sensitivity of some older individuals cannot be ruled out.

This drug is known to be substantially excreted by the kidney, and the risk of toxic reactions to this drug may be greater in patients with impaired renal function. Because elderly patients are more likely to have decreased renal function, care should be taken in dose selection, and it may be useful to monitor renal function.

8.6 Renal Impairment

In the presence of severe renal impairment with or without coexisting hepatic impairment, prolonged dosing intervals for the clarithromycin component may be appropriate.

8.7 Hepatic Impairment

It is recommended to avoid the use of OMECLAMOX-PAK in patients with hepatic impairment [see Clinical Pharmacology (12.3)].

8.8 Asian Patients

It is recommended to avoid the use of OMECLAMOX-PAK in Asian patients unless it is deemed that the benefits outweigh the risks [see Clinical Pharmacology (12.3)].

10 OVERDOSAGE

In case of an overdose, patients should contact a physician, poison control center, or emergency room. There is neither a pharmacologic basis nor data suggesting an increased toxicity of the combination compared to individual components.

As with the management of any overdose, the possibility of multiple drug ingestion should be considered. For current information on treatment of any drug overdose, contact your local Poison Control Center at 1-800-222-1222.

Omeprazole:

Reports have been received of overdosage with omeprazole in humans. Doses ranged up to 2400 mg (120 times the usual recommended clinical dose). Manifestations were variable, but included confusion, drowsiness, blurred vision, tachycardia, nausea, vomiting, diaphoresis, flushing, headache, dry mouth, and other adverse reactions similar to those seen in normal clinical experience [see Adverse Reactions (6.3)]. Symptoms were transient, and no serious clinical outcome has been reported when omeprazole was taken alone. No specific antidote for omeprazole overdosage is known. Omeprazole is extensively protein bound and is, therefore, not readily dialyzable. In the event of overdosage, treatment should be symptomatic and supportive.

Single oral doses of omeprazole at 1350, 1339, and 1200 mg/kg were lethal to mice, rats, and dogs, respectively. Animals given these doses showed sedation, ptosis, tremors, convulsions, and decreased activity, body temperature, and respiratory rate and increased depth of respiration.

Clarithromycin:

Overdosage of clarithromycin can cause gastrointestinal symptoms such as abdominal pain, vomiting, nausea, and diarrhea.

Adverse reactions accompanying overdosage should be treated by the prompt elimination of unabsorbed drug and supportive measures. As with other macrolides, clarithromycin serum concentrations are not expected to be appreciably affected by hemodialysis or peritoneal dialysis.

Amoxicillin:

In case of overdosage, discontinue medication, treat symptomatically, and institute supportive measures as required. If the overdosage is very recent and there is no contraindication, an attempt at emesis or other means of removal of drug from the stomach may be performed. A prospective study of 51 pediatric patients at a poison-control center suggested that overdosages of less than 250 mg/kg of amoxicillin are not associated with significant clinical symptoms and do not require gastric emptying^1.

Interstitial nephritis resulting in oliguric renal failure has been reported in a small number of patients after overdosage with amoxicillin. Crystalluria, in some cases leading to renal failure, has also been reported after amoxicillin overdosage in adult and pediatric patients. In case of overdosage, adequate fluid intake and diuresis should be maintained to reduce the risk of amoxicillin crystalluria. Renal impairment appears to be reversible with cessation of drug administration. High blood concentrations may occur more readily in patients with impaired renal function because of decreased renal clearance of amoxicillin. Amoxicillin can be removed from circulation by hemodialysis.

11 DESCRIPTION

OMECLAMOX-PAK consists of a pack of ten individual daily administration cards, each card containing two omeprazole delayed-release 20 mg capsules, USP, two clarithromycin 500 mg tablets, USP, and four amoxicillin 500 mg capsules, USP, for oral administration.

Omeprazole Delayed-Release Capsules, USP

The active ingredient in omeprazole delayed-release capsules is a substituted benzimidazole, 5-methoxy-2-[[(4-methoxy-3,5-dimethyl- 2-pyridinyl) methyl] sulfinyl]1H-benzimidazole, a proton pump inhibitor that inhibits gastric acid secretion. Its empirical formula is C17H19N3O3S, with a molecular weight of 345.42. The structural formula is:

Omeprazole is a white to off-white crystalline powder that melts with decomposition at about 155°C. It is a weak base, freely soluble in ethanol and methanol, and slightly soluble in acetone and isopropanol, and very slightly soluble in water. The stability of omeprazole is a function of pH; it is rapidly degraded in acid media, but has acceptable stability under alkaline conditions.

Each omeprazole delayed-release capsule contains 20 mg of omeprazole in the form of enteric-coated granules with the following inactive ingredients: crospovidone, hypromellose, lactose, magnesium stearate, mannitol, meglumine, methacrylic acid copolymer, poloxamer, povidone and triethyl acetate. The capsule shells contain: D&C Red #28, FD&C Blue No. 1, FD&C Red No. 40, FD&C Yellow No. 6, yellow iron oxide, gelatin, silicon dioxide, sodium lauryl sulfate and titanium dioxide. Imprinting ink contains: D&C Yellow No. 10 aluminum lake, FD&C Blue No. 1 aluminum lake, FD&C Blue No. 2 aluminum lake, FD&C Red No. 40 aluminum lake, n-butyl alcohol, pharmaceutical glaze, propylene glycol, SDA-3A alcohol and synthetic black iron oxide.

Clarithromycin Tablets, USP

Clarithromycin is a semi-synthetic macrolide antimicrobial. Chemically, it is 6-0-methylerythromycin. The molecular formula is C38H69NO13, and the molecular weight is 747.96. Clarithromycin has the following structural formula:

Clarithromycin is a white to off-white crystalline powder. It is soluble in acetone, slightly soluble in methanol, ethanol, and acetonitrile, and practically insoluble in water. Each tablet for oral administration contains 500 mg of clarithromycin and the following inactive ingredients: croscarmellose sodium, lactose monohydrate, magnesium stearate, microcrystalline cellulose, Opadry II (White), povidone, stearic acid, and talc. Opadry II (White) contains hypromellose, polyethylene glycol, polydextrose, titanium dioxide and triacetin.

Amoxicillin Capsules, USP:

Amoxicillin, a semisynthetic penicillin class antibacterial, is an analogue of ampicillin, with a broad spectrum of bactericidal activity against many gram-positive and gram-negative microorganisms. Chemically it is (2S, 5R, 6R)-6-[(R)-(-)-2-amino-2-(p-hydroxyphenyl)acetamido]- 3,3-dimethyl-7-oxo-4-thia-1-aza-bicyclo[3.2.0] heptane-2-carboxylic acid trihydrate. Its empirical formula is C16H19N3O5S •3H2O with a molecular weight of 419.45. Amoxicillin has the following structural formula:

Amoxicillin capsules contain amoxicillin trihydrate equivalent to 500 mg of amoxicillin. Amoxicillin capsules USP also contain magnesium stearate and sodium lauryl sulfate. The capsule shell contains D&C Red No. 33, FD&C Blue No. 1, FD&C Red No. 40, FD&C Yellow No. 6, gelatin, sodium lauryl sulfate and titanium dioxide. Each 500 mg capsule contains up to 0.0052 mEq (0.119 mg) of sodium.

12 CLINICAL PHARMACOLOGY

12.1 Mechanism of Action

Omeprazole is an antisecretory drug whereas clarithromycin and amoxicillin are antibacterial drugs [see Clinical Pharmacology (12.4)].

12.3 Pharmacokinetics

Pharmacokinetics when all three of the OMECLAMOX-PAK components were coadministered has not been studied. Studies have shown the low risk of clinically significant interactions of omeprazole and amoxicillin or omeprazole and clarithromycin when administered together. There is no information about the gastric mucosal concentrations of omeprazole, clarithromycin and amoxicillin after administration of these drugs concomitantly. The systemic pharmacokinetic information presented below is based on studies in which each product was administered alone, or in combination of two components.

Omeprazole Delayed-Release Capsules, USP

Absorption and Distribution

Omeprazole delayed-release capsules contain an enteric-coated granule formulation of omeprazole (because omeprazole is acid- labile), so that absorption of omeprazole begins only after the granules leave the stomach. Absorption is rapid, with peak plasma concentrations of omeprazole occurring within 0.5 to 3.5 hours. Peak plasma concentrations of omeprazole and AUC are approximately proportional to doses up to 40 mg, but because of a saturable first-pass effect, a greater than linear response in peak plasma concentration and AUC occurs with doses greater than 40 mg. Absolute bioavailability (compared with intravenous administration) is about 30-40% at doses of 20-40 mg, due in large part to presystemic metabolism. In healthy subjects the plasma half-life is 0.5 to 1 hour, and the total body clearance is 500-600 mL/min.

The bioavailability of omeprazole increases slightly upon repeated administration of omeprazole delayed-release capsules.

Omeprazole delayed-release capsules 40 mg was bioequivalent when administered with and without applesauce. However, omeprazole delayed-release capsules 20 mg was not bioequivalent when administered with and without applesauce. When administered with applesauce, a mean 25% reduction in Cmax was observed without a significant change in AUC for omeprazole delayed-release capsules 20 mg. The clinical relevance of this finding is unknown. Protein binding is approximately 95%.

Metabolism and Excretion

Among those females aged 18 to 44 years of age, 22.4% were diagnosed with skin infections and 7.6% had pneumonia.

Geriatric Patients

The elimination rate of omeprazole was somewhat decreased in the elderly, and bioavailability was increased. Omeprazole was 76% bioavailable when a single 40 mg oral dose of omeprazole (buffered solution) was administered to healthy elderly volunteers, versus 58% in young volunteers given the same dose. Nearly 70% of the dose was recovered in urine as metabolites of omeprazole and no unchanged drug was detected. The plasma clearance of omeprazole was 250 mL/min (about half that of young volunteers) and its plasma half-life averaged one hour, about twice that of young healthy volunteers.

Hepatic Impairment

In patients with chronic hepatic disease, the bioavailability of omeprazole increased to approximately 100% compared with an IV dose, reflecting decreased first-pass effect, and the plasma half-life of the drug increased to nearly 3 hours compared with the half-life in normals of 0.5-1 hour. Plasma clearance averaged 70 mL/min, compared with a value of 500-600 mL/min in normal subjects. It is recommended to avoid the use of OMECLAMOX-PAK in patients with hepatic impairment.

Renal Impairment

In patients with chronic renal impairment, whose creatinine clearance ranged between 10 and 62 mL/min/1.73m^2, the disposition of omeprazole was very similar to that in healthy volunteers, although there was a slight increase in bioavailability. Because urinary excretion is a primary route of excretion of omeprazole metabolites, their elimination slowed in proportion to the decreased creatinine clearance. No dose reduction is necessary in patients with renal impairment.

Asian Patients

In pharmacokinetic studies of single 20 mg omeprazole doses, an increase in AUC of approximately four-fold was noted in Asian subjects compared with Caucasians. It is recommended to avoid the use of OMECLAMOX-PAK in Asian patients unless it is deemed that the benefits outweigh the risks.

Clarithromycin Tablets, USP

Clarithromycin is rapidly absorbed from the gastrointestinal tract after oral administration. The absolute bioavailability of 250 mg clarithromycin tablets was approximately 50%. For a single 500 mg dose of clarithromycin, food slightly delays the onset of clarithromycin absorption, increasing the peak time from approximately 2 to 2.5 hours. Food also increases the clarithromycin peak plasma concentration by about 24%, but does not affect the extent of clarithromycin bioavailability. Food does not affect the onset of formation of the antimicrobially active metabolite, 14-OH clarithromycin or its peak plasma concentration but does slightly increase the extent of metabolite formation, indicated by an 11% decrease in area under the plasma concentration-time curve (AUC). Therefore, clarithromycin tablets may be given without regard to food.

In nonfasting healthy human subjects (males and females), peak plasma concentrations were attained within 2 to 3 hours after oral dosing. Steady-state peak plasma clarithromycin concentrations were attained within 3 days and were approximately 3 to 4 μg/mL with a 500 mg dose administered every 8 to 12 hours. The elimination half-life of clarithromycin was 5 to 7 hours with 500 mg administered every 8 to 12 hours. The nonlinearity of clarithromycin pharmacokinetics is slight at the recommended dose of 500 mg administered every 8 to 12 hours. With a 500 mg every 8 to 12 hours dosing, the peak steady-state concentration of 14-OH clarithromycin is up to 1 μg/mL, and its elimination half-life is about 7 to 9 hours. The steady-state concentration of this metabolite is generally attained within 3 to 4 days.

After a 500 mg tablet every 12 hours, the urinary excretion of clarithromycin is approximately 30%. The renal clearance of clarithromycin approximates the normal glomerular filtration rate. The major metabolite found in urine is 14-OH clarithromycin, which accounts for an additional 10% to 15% of the dose with a 500 mg tablet administered every 12 hours.

The steady-state concentrations of clarithromycin in subjects with impaired hepatic function did not differ from those in normal subjects; however, the 14-OH clarithromycin concentrations were lower in the hepatically impaired subjects. The decreased formation of 14-OH clarithromycin was at least partially offset by an increase in renal clearance of clarithromycin in the subjects with impaired hepatic function when compared to healthy subjects.

The pharmacokinetics of clarithromycin was altered in subjects with impaired renal function. In the presence of severe renal impairment with or without coexisting hepatic impairment, prolonged dosing intervals for clarithromycin may be appropriate.

Amoxicillin Capsules, USP

Amoxicillin is stable in the presence of gastric acid and may be given without regard to meals. It is rapidly absorbed after oral administration. It diffuses readily into most body tissues and fluids, with the exception of brain and spinal fluid, except when meninges are inflamed. The half-life of amoxicillin is 61.3 minutes. Most of the amoxicillin is excreted unchanged in the urine; its excretion can be delayed by concurrent administration of probenecid. In blood serum, amoxicillin is approximately 20% protein- bound.

Orally administered doses of 500 mg amoxicillin capsules result in average peak blood concentrations 1 to 2 hours after administration in the range of 5.5 μg /mL to 7.5 μg /mL. Detectable serum concentrations are observed up to 8 hours after an orally administered dose of amoxicillin. Approximately 60% of an orally administered dose of amoxicillin is excreted in the urine within 6 to 8 hours.

Combination Therapy of Omeprazole with Antimicrobials:

Omeprazole 40 mg daily was given in combination with clarithromycin 500 mg every 8 hours to healthy adult male subjects. The steady-state plasma concentrations of omeprazole were increased (Cmax, AUC0-24, and T1/2 increases of 30%, 89% and 34% respectively) by the concomitant administration of clarithromycin. The observed increases in omeprazole plasma concentration were associated with the following pharmacological effects. The mean 24-hour gastric pH value was 5.2 when omeprazole was administered alone and 5.7 when coadministered with clarithromycin.

The plasma concentrations of clarithromycin and 14-hydroxy-clarithromycin were increased by the concomitant administration of omeprazole. For clarithromycin, the mean Cmax was 10% greater, the mean Cmin was 27% greater, and the mean AUC0-8 was 15% greater when clarithromycin was administered with omeprazole than when clarithromycin was administered alone. Similar results were seen for 14-hydroxy-clarithromycin, the mean Cmax was 45% greater, the mean Cmin was 57% greater, and the mean AUC0-8 was 45% greater. Clarithromycin concentrations in the gastric tissue and mucus were also increased by concomitant administration of omeprazole.

Table 1 Mean ± SD Clarithromycin Tissue Concentrations 2 Hours after Dose
Tissue | Clarithromycin (μg/g) | Clarithromycin + Omeprazole (μg/g)
Antrum | 10.48 ± 2.01 (n = 5) | 19.96 ± 4.71 (n = 5)
Fundus | 20.81 ± 7.64 (n = 5) | 24.25 ± 6.37 (n = 5)
Mucus | 4.15 ± 7.74 (n = 4) | 39.29 ± 32.79 (n = 4)

Drug Interactions

Antiretroviral Drugs and Omeprazole

The clinical importance and the mechanisms behind interactions between omeprazole and antiretroviral drugs are not always known. Increased gastric pH during omeprazole treatment may change the absorption of the antiretroviral drug. Other possible interaction mechanisms are via inhibition of CYP2C19.

Following multiple doses of nelfinavir (1250 mg twice daily) and omeprazole (40 mg once daily), AUC of nelfinavir and the M8 metabolite was decreased by 36% and 92%, Cmax by 37% and 89% and Cmin by 39% and 75%.

Following multiple doses of atazanavir (400 mg once daily) and omeprazole (40 mg once daily 2 hours before atazanavir), AUC of atazanavir was decreased by 94%, Cmax by 96%, and Cmin by 95%. Concomitant administration with omeprazole and atazanavir is not recommended.

Saquinavir serum AUC, Cmax and Cmin increased by 82%, 75% and 106%, respectively, following multiple dosing of saquinavir/ritonavir (1000/100 mg) twice daily for 15 days with omeprazole 40 mg once daily coadministered days 11 to 15 [see Drug Interactions (7.6)].

Cilostazol and Omeprazole

Omeprazole acts as an inhibitor of CYP2C19. Omeprazole, given in doses of 40 mg daily for one week to 20 healthy subjects in crossover study, increased Cmax and AUC of cilostazol by 18% and 26% respectively. Cmax and AUC of one of its active metabolites, 3,4-dihydro-cilostazol, which has 4-7 times the activity of cilostazol, were increased by 29% and 69% respectively. Co-administration of cilostazol with omeprazole is expected to increase concentrations of cilostazol and its above mentioned active metabolite. Therefore a dose reduction of cilostazol from 100 mg b.i.d. to 50 mg b.i.d. should be considered [see Drug Interactions (7.7)].

Theophylline and Clarithromycin

Theophylline is metabolized by CYP1A2 and CYP3A4. Clarithromycin will increase theophylline plasma concentrations when it is administered concomitantly. In two studies in which theophylline was administered with clarithromycin (theophylline sustained- release formulation dosed at either 6.5 mg/kg or 12 mg/kg together with 250 or 500 mg every 12 hours clarithromycin), the steady-state Cmax, Cmin, and AUC of theophylline increased about 20%. Monitoring of serum theophylline concentrations should be considered for patients receiving high doses of theophylline or with baseline concentrations in the upper therapeutic range [see Drug Interactions (7.9)].

Voriconazole and Omeprazole

Voriconazole is an inhibitor of CYP2C19, CYP2C9, and CYP3A4. Coadministration of voriconazole and omeprazole will increase omeprazole plasma exposure. When voriconazole (400 mg every 12 hours x 1 day, then 200 mg x 6 days) was given with omeprazole (40 mg once daily x 7 days) to healthy subjects, it significantly increased the steady-state Cmax and AUC0-24 of omeprazole, an average of 2 times (90% CI: 1.8, 2.6) and 4 times (90% CI: 3.3, 4.4) respectively as compared to when omeprazole was given without voriconazole. Dose adjustment of omeprazole is not normally required.

Mycophenolate mofetil

Administration of omeprazole 20 mg twice daily for 4 days and a single 1000 mg dose of mycophenolate mofetil approximately one hour after the last dose of omeprazole to 12 healthy subjects in a cross-over study resulted in a 52% reduction in the Cmax and 23% reduction in the AUC of mycophenolic acid.

12.4 Microbiology

Mechanism of Action

Omeprazole, an antisecretory drug with the substituted benzimidazoles, suppresses gastric acid secretion by specific inhibition of the H+/K+ ATPase enzyme system at the secretory surface of the gastric parietal cell. Because this enzyme system is regarded as the acid (proton) pump within the gastric mucosa, omeprazole has been characterized as a gastric acid-pump inhibitor, in that it blocks the final step of acid production. This effect is dose-dependent and leads to inhibition of both basal and stimulated acid secretion irrespective of the stimulus. Omeprazole can also exhibit anti-bacterial activity depending on the culture conditions. Animal studies indicate that after rapid disappearance from plasma, omeprazole can be found within the gastric mucosa for a day or more.

Clarithromycin exerts its antibacterial activity by binding to the 50S ribosomal subunit of susceptible microorganisms resulting in inhibition of protein synthesis.

Amoxicillin acts through the inhibition of biosynthesis of cell wall mucopeptide.

Triple therapy with omeprazole, clarithromycin and amoxicillin has been shown to be active against most strains of Helicobacter pylori in vitro and in clinical infections as indicated [see Indications and Usage (1)].

Interactions with Other Antibacterial Drugs

In vitro studies show that chloramphenicol, macrolides, sulfonamides, and tetracyclines may interfere with bactericidal effects of penicillin; however, the clinical significance of this interaction is not well documented.

Drug Resistance

Helicobacter pylori Pretreatment Resistance

Clarithromycin pretreatment resistance rates were 9.3% (41/439) in omeprazole/clarithromycin/amoxicillin triple therapy studies [see Clinical Studies (14.1)].

Amoxicillin pretreatment susceptible isolates (≤ 0.25 μg/mL) were found in 99.3% (436/439) of the patients in the omeprazole/clarithromycin/amoxicillin triple therapy studies [see Clinical Studies (14)].)

Effects on Gastrointestinal Microbial Ecology:

Decreased gastric acidity due to any means including proton pump inhibitors, increases gastric counts of bacteria normally present in the gastrointestinal tract. Treatment with proton pump inhibitors may lead to slightly increased risk of gastrointestinal infections such as Salmonella and Campylobacter.

Susceptibility Testing

For specific information regarding susceptibility test interpretive criteria and associated test methods and quality control standards recognized by FDA for this drug, please see: https://www.fda.gov/STIC.

13 NONCLINICAL TOXICOLOGY

13.1 Carcinogenesis, Mutagenesis, Impairment of Fertility

Omeprazole:

Carcinogenicity

In two 24-month carcinogenicity studies in rats, omeprazole at daily doses of 1.7, 3.4, 13.8, 44.0 and 140.8 mg/kg/day (about 0.7 to 57 times a human dose of 20 mg/day, as expressed on a body surface area basis) produced gastric ECL cell carcinoids in a dose-related manner in both males and females; the incidence of this effect was markedly higher in female rats, which had higher blood concentrations of omeprazole. Gastric carcinoids seldom occur in the untreated rat. In addition, ECL cell hyperplasia was present in all treated groups of both sexes. In one of these studies, female rats were treated with 13.8 mg omeprazole/kg/day (about 6 times a human dose of 20 mg/day, based on body surface area) for one year, and then followed for an additional year without the drug. No carcinoids were seen in these rats. An increased incidence of treatment-related ECL cell hyperplasia was observed at the end of one year (94% treated vs. 10% controls). By the second year the difference between treated and control rats was much smaller (46% vs. 26%) but still showed more hyperplasia in the treated group. Gastric adenocarcinoma was seen in one rat (2%). No similar tumor was seen in male or female rats treated for two years. For this strain of rat no similar tumor has been noted historically, but a finding involving only one tumor is difficult to interpret.

In a 52-week toxicity study in Sprague-Dawley rats, brain astrocytomas were found in a small number of males that received omeprazole at dose levels of 0.4, 2, and 16 mg/kg/day (about 0.2 to 6.5 times the human dose on a body surface area basis). No astrocytomas were observed in female rats in this study or in males or females from a 2-year carcinogenicity study in Sprague-Dawley rats at the high dose of 140.8 mg/kg/day (about 57 times the human dose on a body surface area basis). A 78-week mouse carcinogenicity study of omeprazole did not show increased tumor occurrence, but the study was not conclusive. A 26-week p53 (+/–) transgenic mouse carcinogenicity study was not positive.

Genotoxicity

Omeprazole was positive for clastogenic effects in an in vitro human lymphocyte chromosomal aberration assay, in one of two in vivo mouse micronucleus tests, and in an in vivo bone marrow cell chromosomal aberration assay. Omeprazole was negative in the in vitro Ames test, an in vitro mouse lymphoma cell forward mutation assay, and an in vivo rat liver DNA damage assay.

Impairment of Fertility

Omeprazole at oral doses up to 138 mg/kg/day in rats (about 56 times the human dose on a body surface area basis) was found to have no effect on fertility and reproductive performance.

Clarithromycin:

Carcinogenicity

Carcinogencity studies have not been conducted with clarithromycin.

The following in vitro mutagenicity tests have been conducted with clarithromycin:

- Bacterial reverse-mutation test (Ames test)
- Salmonella/Mammalian Microsomes Test
- Bacterial Induced Mutation Frequency Test
- In Vitro Chromosome Aberration Test
- Rat Hepatocyte DNA Synthesis Assay
- Mouse Lymphoma Assay
- Mouse Dominant Lethal Study
- Mouse Micronucleus Test

All tests had negative results except the in vitro chromosome aberration test which was positive in one test and negative in another.

Impairment of Fertility

Fertility and reproduction studies have shown that daily doses of clarithromycin up to 160 mg/kg/day to male and female rats caused no adverse effects on the estrous cycle, fertility, parturition, or number and viability of offspring. Plasma level sin rats after 150 mg/kg/day were twice the human serum levels.

Testicular atrophy occurred in rats at doses 7 times, in dogs at doses 3 times, and in monkeys at doses 8 times the maximum human daily dose (on a body surface area basis).

Amoxicillin:

Carcinogenicity

Carcinogenicity studies have not been conducted with amoxicillin.

Genotoxicity

The genotoxicity of amoxicillin has not been assessed.

Impairment of Fertility

In a multi-generation reproduction study in rats, no impairment of fertility or other adverse reproductive effects were seen at doses up to 500 mg/kg (approximately 2 times the 3 g human dose).

14 CLINICAL STUDIES

14.1 H. pylori associated Duodenal Ulcer Disease

Three U.S., randomized, double-blind clinical studies in patients with H. pylori infection and duodenal ulcer disease (n = 558) compared omeprazole plus clarithromycin plus amoxicillin with clarithromycin plus amoxicillin. Two studies (1 and 2) were conducted in patients with an active duodenal ulcer, and the other study (3) was conducted in patients with a history of a duodenal ulcer in the past 5 years but without an ulcer present at the time of enrollment. The dose regimen in the studies was omeprazole 20 mg twice daily plus clarithromycin 500 mg twice daily plus amoxicillin 1 g twice daily for 10 days; or clarithromycin 500 mg twice daily plus amoxicillin 1 g twice daily for 10 days. In studies 1 and 2, patients who took the omeprazole regimen also received an additional 18 days of omeprazole 20 mg once daily. Endpoints studied were eradication of H. pylori and duodenal ulcer healing (studies 1 and 2 only). H. pylori status was determined by CLOtest®, histology and culture in all three studies. For a given patient, H. pylori was considered eradicated if at least two of these tests were negative and none was positive.

The combination of omeprazole plus clarithromycin plus amoxicillin, was effective in eradicating H. pylori.

Table 2 Per-Protocol and Intent-to-Treat H. pylori Eradication Rates - % of Patients Cured [95% Confidence Interval]
Per-Protocol and Intent-to-Treat H. pylon Eradication Rates
% of Patients Cured [95% Confidence Interval]
 | omeprazole + chlarithromycin + amoxicillin |  | chlarithromycin + amoxicillin
 | Per-Protocol† | Intent-to-Treat‡ | Per-Protocol† | Intent-to-Treat‡
Study 1 | *77 [64, 86] (n = 64) | *69 [57, 79] (n = 80) | 43 [31, 56] (n = 67) | 37 [27, 38] (n = 84)
Study 2 | *78 [67, 88] (n = 65) | *73 [61, 82] (n = 77) | 41 [29, 54] (n = 68) | 36 [26, 47] (n = 83)
Study 3 | *90 [80, 96] (n = 69) | *83 [74, 91] (n = 84) | 33 [24, 44] (n = 93) | 32 [23, 42] (n = 99)
†Patients were included in the analysis if they had confirmed duodenal ulcer disease (active ulcer, studies 1 and 2; history of ulcer within 5 years, study 3) and H. pylori infection at baseline defined as at least two of three positive endoscopic tests from CLOtest®, histology, and/or culture. Patients were included in the analysis if they completed the study. Additionally, if patients dropped out of the study due to an adverse event related to the study drug, they were included in the analysis as failures of therapy. The impact of eradication on ulcer recurrence has not been assessed in patients with a past history of ulcer.
‡Patients were included in the analysis if they had documented H. pylori infection at baseline and had confirmed duodenal ulcer disease. All dropouts were included as failures of therapy.
*(p < 0.05) versus clarithromycin plus amoxicillin.

15 REFERENCES

1. Swanson-Biearman B, Dean BS, Lopez G, Krenzelok EP. The effects of penicillin and cephalosporin ingestions in children less than six years of age. Vet Hum Toxicol. 1988;30:66-67.

16 HOW SUPPLIED/STORAGE AND HANDLING

OMECLAMOX-PAK is supplied in a carton containing ten individual daily administration cards. Each card contains the morning dose and the evening dose of the following three drugs:

Omeprazole Delayed-Release Capsules, USP, 20 mg

- Two opaque hard gelatin lavender and grey capsules, with ‘R 158’ and ‘OMEPRAZOLE 20 mg’ imprinted on the capsules in black ink, containing off-white to pale-yellow, elliptical spherical pellets.

Clarithromycin Tablets, USP, 500 mg

- Two white, biconvex beveled-edge capsule-shaped coated tablets debossed with ‘54 312’ on one side and plain on the other side.

Amoxicillin Capsules, USP, 500 mg

- Four opaque hard gelatin yellow capsules, marked ’GG849’. Each capsule contains amoxicillin trihydrate equivalent to 500 mg amoxicillin.

NDC 66220-422-02 | Carton containing 10 daily administration cards
NDC 66220-422-01 | Daily administration card

Store at controlled room temperature between 20°C and 25°C (68°F and 77°F). Protect from light and moisture.

17 PATIENT COUNSELING INFORMATION

Administration

Inform patients that each dose of OMECLAMOX-PAK contains four pills: one opaque lavender/grey capsule (omeprazole), one white tablet (clarithromycin) and two opaque yellow capsules (amoxicillin).

Take each dose of four pills in the morning and four pills in the evening before eating a meal, for 10 days. Capsules and tablets should not be crushed or chewed, and should be swallowed whole [see Dosage and Administration (2)].

Embryo-Fetal Toxicity

Advise females of reproductive potential that that if pregnancy occurs while taking this OMECLAMOX-PAK, there is a potential hazard to the fetus [see Warnings and Precautions (5.1) and Use in Specific Populations (8.1)].

Drug Interactions

Patients should be advised to report to their doctor the use of any other medications while taking OMECLAMOX-PAK [see Drug Interactions (7)].

The simultaneous administration of any of the following drugs with OMECLAMOX-PAK may result in clinically significant adverse reactions or even death:

- Colchicine
- Ergotamine/dihydroergotamine
- Pimozide
- Lurasidone
- Antiarrhythmic drugs (e.g., quinidine, disopyramide)
- Digoxin
- Anticoagulants (e.g., warfarin)
- Atazanavir
- Nelfinavir
- Saquinavir
- Cilostazol
- Tacrolimus
- Theophylline
- Carbamazepine
- Sildenafil
- HMG-CoA reductase inhibitors (also known as statins)
- Triazolobenzodiazepines (e.g., triazolam and alprazolam) and related benzodiazepines (e.g., midazolam)
- Probenecid
- Drugs for which gastric pH can affect bioavailability

Diarrhea

Advise patients that diarrhea is a common problem caused by omeprazole and antibiotics that usually ends when the drug is discontinued. Sometimes after starting treatment, patients can develop severe diarrhea with watery and bloody stools (with or without stomach cramps and fever) even as late as two or more months after having taken the last dose of the drug. If this occurs, patients should contact a physician as soon as possible [see Warnings and Precautions (5.4)].

Acute Tubulointerstitial Nephritis

Advise the patient or caregiver to call the patient's healthcare provider immediately if they experience signs and/or symptoms associated with acute tubulointerstitial nephritis [see Warnings and Precautions (5.7)].

Cutaneous or Systemic Lupus

Advise patients to report any symptoms associated with cutaneous or systemic lupus erythematosus [see Warnings and Precautions (5.8)].

Antibacterial Resistance

Patients should be counseled that antibacterial drugs including OMECLAMOX-PAK should only be used to treat bacterial infections. They do not treat viral infections (e.g., the common cold). When OMECLAMOX-PAK is prescribed to treat a bacterial infection, patients should be told that although it is common to feel better early in the course of therapy, the medication should be taken exactly as directed. Skipping doses or not completing the full course of therapy may (1) decrease the effectiveness of the immediate treatment and (2) increase the likelihood that bacteria will develop resistance and will not be treatable by OMECLAMOX-PAK or other antibacterial drugs in the future.

Severe Cutaneous Adverse Reactions

Advise patients about the signs and symptoms of serious skin manifestations. Instruct patients to stop taking OMECLAMOX-PAK immediately and promptly report the first signs or symptoms of skin rash, mucosal lesions, or any other sign of hypersensitivity [see WARNINGS AND PRECAUTIONS (5.2)].

OMECLAMOX-PAK is manufactured for CUMBERLAND PHARMACEUTICALS INC., Nashville, TN 37203.